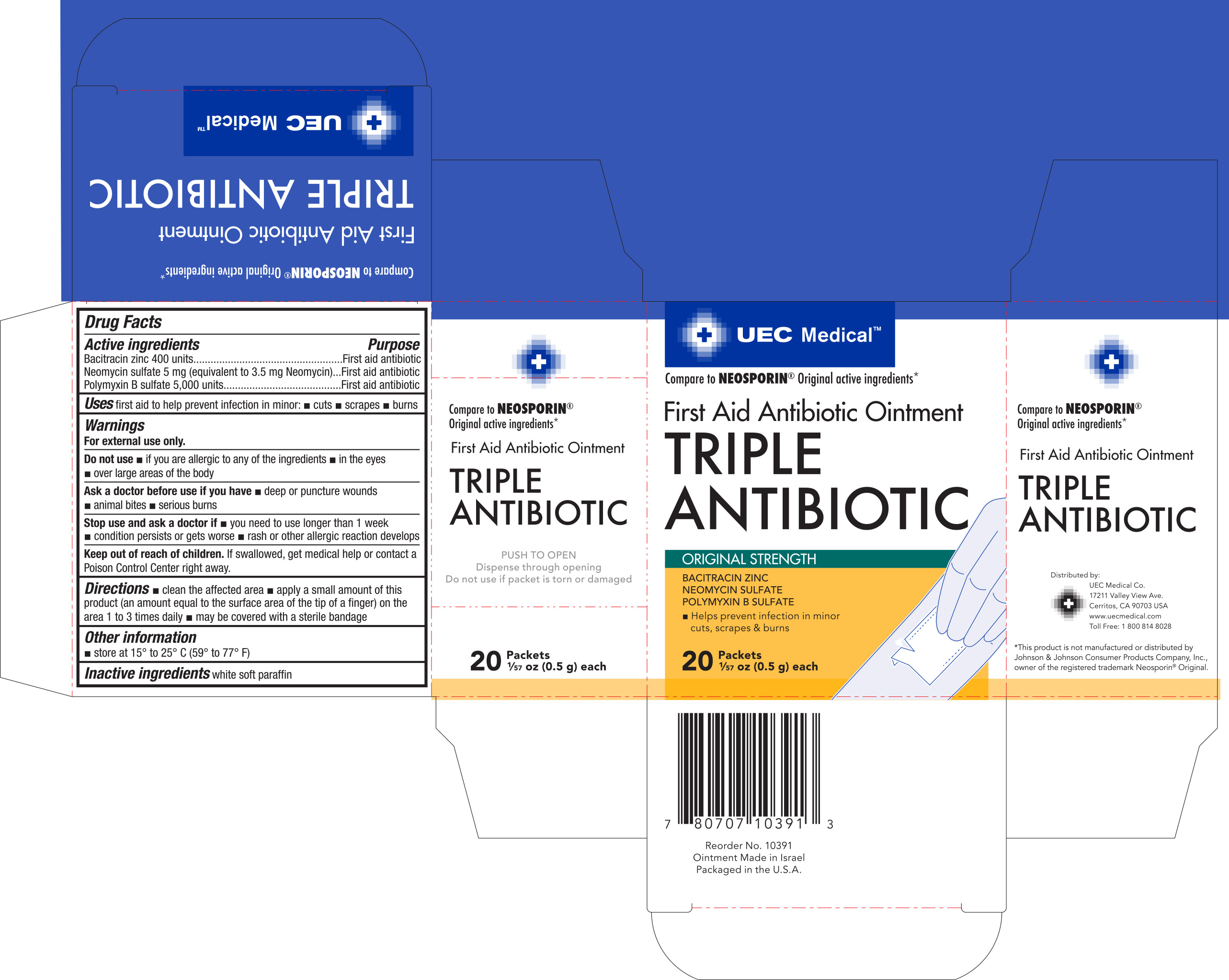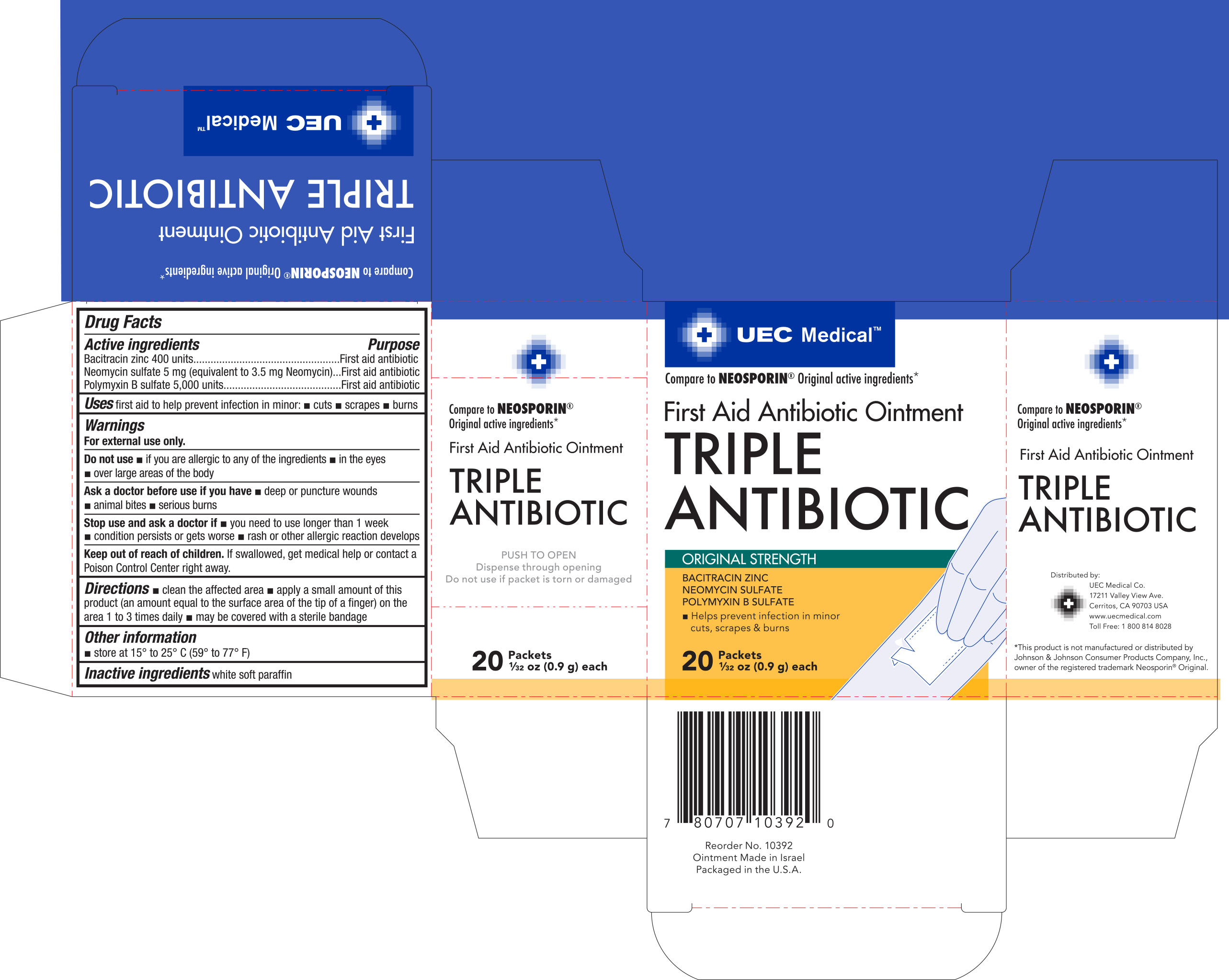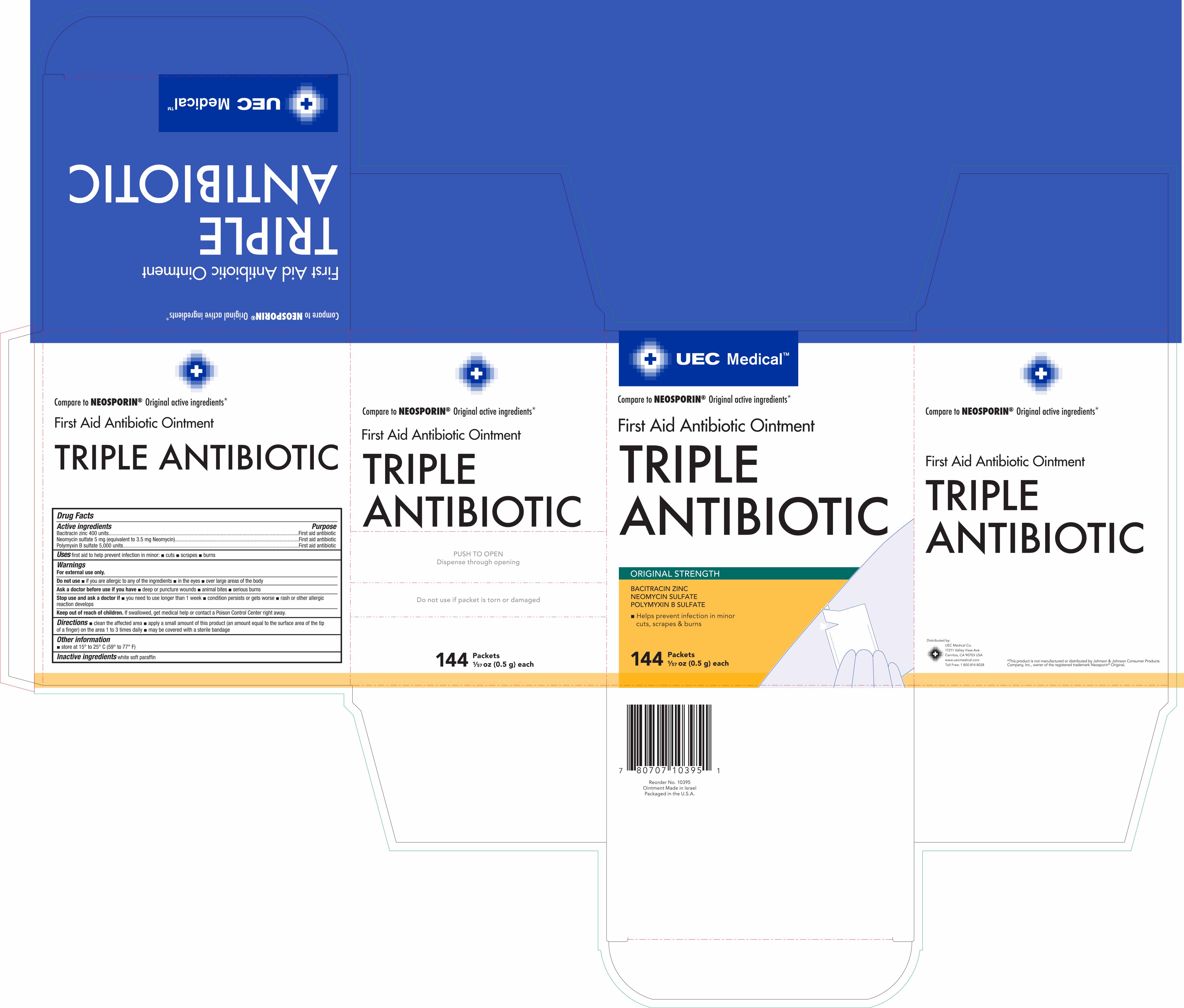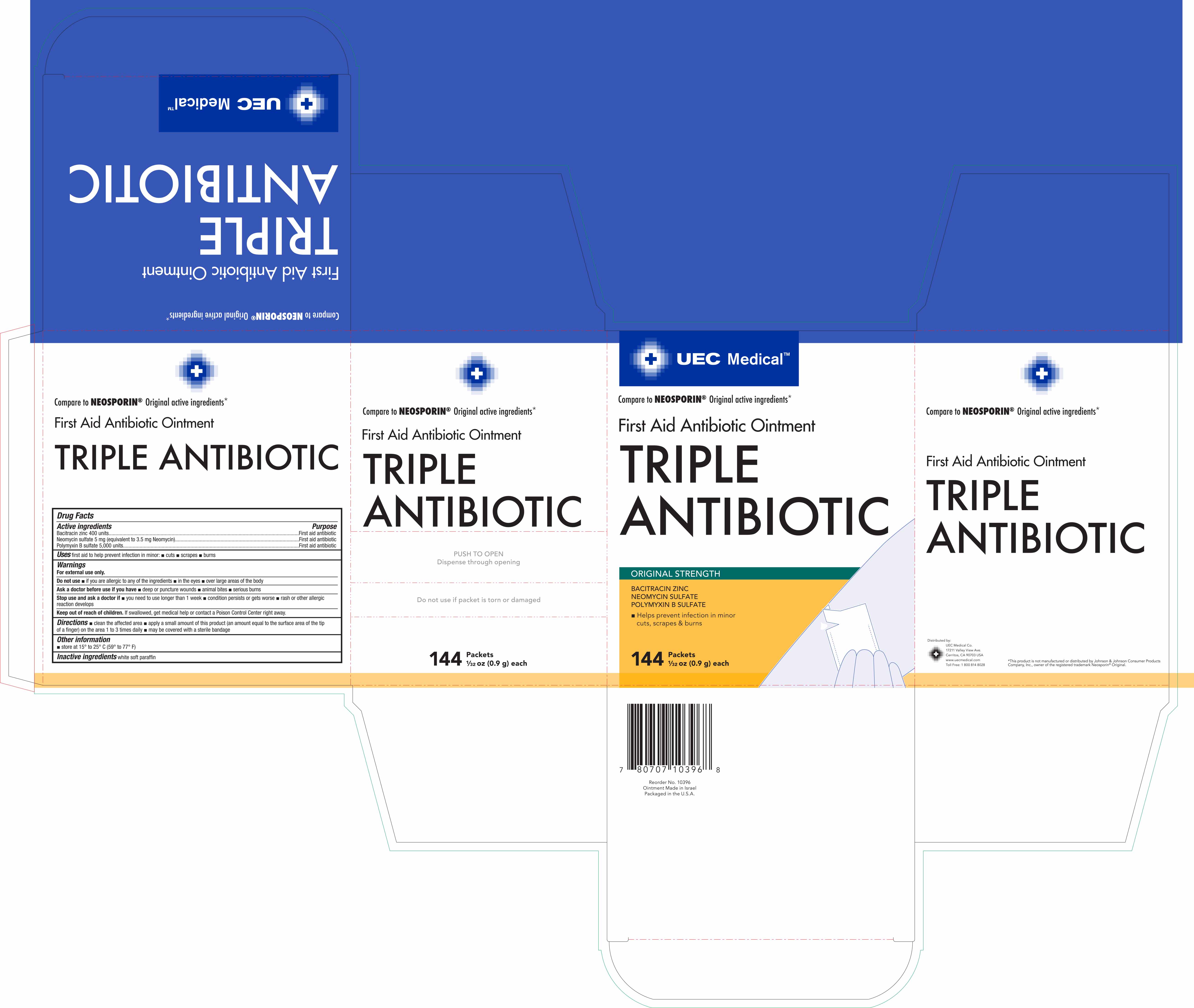 DRUG LABEL: UEC Medical First Aid Antibiotic
NDC: 65923-391 | Form: OINTMENT
Manufacturer: United Exchange Corp.
Category: otc | Type: HUMAN OTC DRUG LABEL
Date: 20180406

ACTIVE INGREDIENTS: NEOMYCIN SULFATE 3.5 mg/1 g; POLYMYXIN B SULFATE 5000 [iU]/1 g; BACITRACIN ZINC 400 [iU]/1 g
INACTIVE INGREDIENTS: PARAFFIN

UEC Medical Triple Antibiotic Ointment 0.5g NBE Neosporin 20 and 144 ct- 10391 and 10395 (2018)

Active ingredients Purpose

Bacitracin zinc 400 units..............................................................First aid antibiotic

Neomycin sulfate 5 mg (equivalent to 3.5 mg Neomycin)............First aid antibiotic

Polymyxin B sulfate 5,000 units...................................................First aid antibiotic

Uses

first aid to help prevent infection in minor:

- cuts
- scrapes
- burns

Warnings

For external use only.

Do not use

- if you are allergic to any of the ingredients
- in the eyes
- over large areas of the body

Ask a doctor before use if you have

- deep or puncture wounds
- animal bites
- serious burns

Stop use and ask a doctor if

- you need to use longer than 1 week
- condition persists or gets worse
- rash or other allergic reaction develops

Keep out of reach of children. If swallowed, get medical help or contact a Poison Control Center right away.

Directions

- clean the affected area
- apply a small amount of this product (an amount equal to the surface area of the tip of a finger) on the area 1 to 3 times daily
- may be covered with a sterile bandage

Other information

- store at 15° to 25°C (59° to 77°F)

Inactive ingredients

white soft paraffin

DOSAGE AND ADMINISTRATION

Distributed by:

UEC Medical

17211 Valley View Ave.

Cerritos, CA 90703